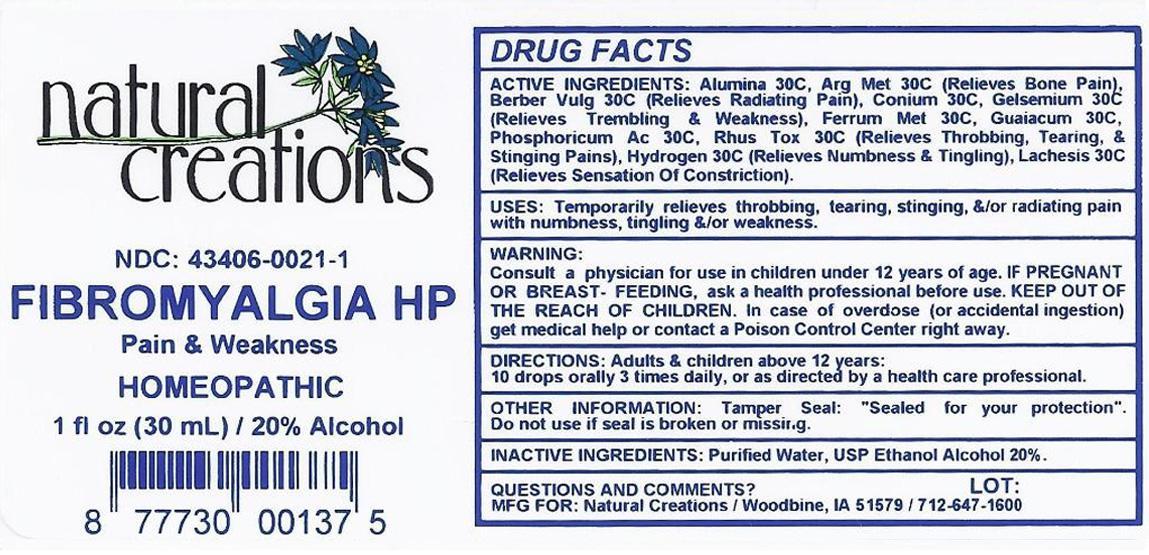 DRUG LABEL: FIBROMYALGIA HP
NDC: 43406-0021 | Form: LIQUID
Manufacturer: Natural Creations, Inc.
Category: homeopathic | Type: HUMAN PRESCRIPTION DRUG LABEL
Date: 20121101

ACTIVE INGREDIENTS: ALUMINUM OXIDE 30 [hp_C]/1 mL; SILVER NITRATE 30 [hp_C]/1 mL; BERBERIS VULGARIS FRUIT 30 [hp_C]/1 mL; CONIUM MACULATUM FLOWERING TOP 30 [hp_C]/1 mL; IRON 30 [hp_C]/1 mL; GELSEMIUM SEMPERVIRENS ROOT 30 [hp_C]/1 mL; GUAIACUM OFFICINALE RESIN 30 [hp_C]/1 mL; HYDROGEN 30 [hp_C]/1 mL; LACHESIS MUTA VENOM 30 [hp_C]/1 mL; PHOSPHORIC ACID 30 [hp_C]/1 mL; TOXICODENDRON PUBESCENS LEAF 30 [hp_C]/1 mL
INACTIVE INGREDIENTS: WATER; ALCOHOL

FIBROMYALGIA HP

ACTIVE INGREDIENT

ACTIVE INGREDIENTS: Alumina 30C, Argentum Metallicum 30C, Berberis Vulgaris 30C, Conium Maculatum 30C, Ferrum Metallicum 30C, Gelsemium Sempervirens 30C, Guaiacum 30C, Hydrogen 30C, Lachesis Mutus 30C, Phosphoricum Acidum 30C, Rhus Toxicodendron 30C

INDICATIONS AND USAGE

USES: Temporarily relieves throbbing, tearing, stinging, &/or radiating pain with numbness, tingling &/or weakness.

WARNING:

Consult a physician for use in children under 12 years of age. IF PREGNANT OR BREAST-FEEDING, ask a health care professional before use. KEEP OUT OF THE REACH OF CHILDREN. In case of overdose (or accidental ingestion) get medical help or contact a Poison Control Center right away.

DOSAGE AND ADMINISTRATION

DIRECTIONS: Adults and children above 12 years: 10 drops orally 3 times daily, or as directed by a health care professional.

OTHER INFORMATION: Tamper Seal: "Sealed for your protection."

Do not use if seal is broken or missing.

INACTIVE INGREDIENTS: Purified Water, USP Ethanol Alcohol 20%

QUESTIONS AND COMMENTS?

MFG FOR: Natural Creations / Woodbine, IA / 51579 712.647.1600

LOT:

PURPOSE

USES: Temporarily relieves throbbing, tearing, stinging, &/or radiating pain with numbness, tingling &/or weakness.

KEEP OUT OF REACH OF CHILDREN

KEEP OUT OF THE REACH OF CHILDREN. In case of overdose (or accidental ingestino) get medical help or contact a Poison Control Center.

PACKAGE LABEL

NDC: 43406-0021-1

FIBROMYALGIA HP

Pain & Weakness

HOMEOPATHIC
1 fl oz (30 mL) / 20% Alcohol

UPC: 877730001375